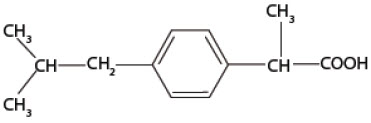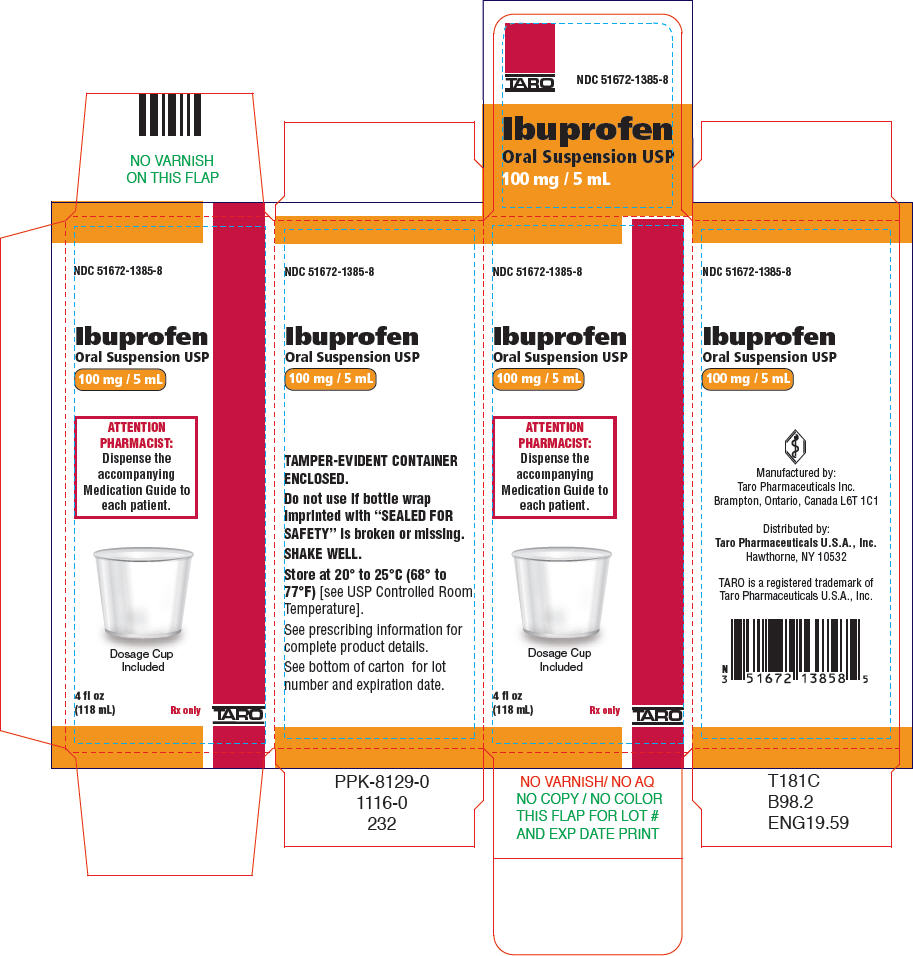 DRUG LABEL: Ibuprofen
NDC: 51672-1385 | Form: SUSPENSION
Manufacturer: Sun Pharmaceutical Industries, Inc.
Category: prescription | Type: HUMAN PRESCRIPTION DRUG LABEL
Date: 20251227

ACTIVE INGREDIENTS: IBUPROFEN 100 mg/5 mL
INACTIVE INGREDIENTS: ACESULFAME POTASSIUM; ANHYDROUS CITRIC ACID; GLYCERIN; POLYSORBATE 80; SODIUM BENZOATE; WATER; SUCROSE; XANTHAN GUM

Ibuprofen
Oral Suspension USP, 100 mg/5 mL

Rx only

BOXED WARNING

Cardiovascular Thrombotic Events

- Nonsteroidal anti-inflammatory drugs (NSAIDs) cause an increased risk of serious cardiovascular thrombotic events, including myocardial infarction and stroke, which can be fatal. This risk may occur early in treatment and may increase with duration of use (see WARNINGSand PRECAUTIONS).
- Ibuprofen oral suspension is contraindicated in the setting of coronary artery bypass graft (CABG) surgery (see CONTRAINDICATIONSand WARNINGS).

Gastrointestinal Risk

- NSAIDs cause an increased risk of serious gastrointestinal adverse events including bleeding, ulceration, and perforation of the stomach or intestines, which can be fatal. These events can occur at any time during use and without warning symptoms. Elderly patients are at greater risk for serious gastrointestinal events (see WARNINGS).

DESCRIPTION

The active ingredient in ibuprofen oral suspension USP is ibuprofen, which is a member of the propionic acid group of nonsteroidal anti-inflammatory drugs (NSAIDs). Ibuprofen is a racemic mixture of [+]S- and [-]R-enantiomers. It is a white to off-white crystalline powder, with a melting point of 74° to 77°C. It is practically insoluble in water (< 0.1 mg/mL), but readily soluble in organic solvents such as ethanol and acetone. Ibuprofen, USP has a pKa of 4.43 ± 0.03 and an n-octanol/water partition coefficient of 11.7 at pH 7.4. The chemical name for ibuprofen is (±)-2-(p-Isobutylphenyl) propionic acid. The molecular weight of ibuprofen is 206.28. Its molecular formula is C13H18O2and it has the following structural formula:

Ibuprofen oral suspension USP is a sucrose-sweetened, white to off-white, berry-flavored suspension containing 100 mg of ibuprofen in 5 mL (20 mg/mL). Inactive ingredients include: acesulfame potassium, berry flavor natural & artificial, citric acid anhydrous, glycerin, pregelatinized modified starch, polysorbate 80, sodium benzoate, purified water, sucrose, xanthan gum.

Meets USP Dissolution Test 2.

CLINICAL PHARMACOLOGY

Pharmacodynamics

Ibuprofen is a nonsteroidal anti-inflammatory drug (NSAID) that possesses anti-inflammatory, analgesic and antipyretic activity. Its mode of action, like that of other NSAIDs, is not completely understood, but may be related to prostaglandin synthetase inhibition. After absorption of the racemic ibuprofen, the [-]R-enantiomer undergoes interconversion to the [+]S-form. The biological activities of ibuprofen are associated with the [+]S-enantiomer.

In a healthy volunteer study, ibuprofen 400 mg given once daily, administered 2 hours prior to immediate-release aspirin (81 mg) for 6 days, showed an interaction with the antiplatelet activity of aspirin as measured by % serum thromboxane B2 (TxB2) inhibition at 24 hours following the day-6 aspirin dose [53%]. An interaction was still observed, but minimized, when ibuprofen 400 mg given once-daily was administered as early as 8 hours prior to the immediate-release aspirin dose [90.7%]. However, there was no interaction with the antiplatelet activity of aspirin when ibuprofen 400 mg, given once daily, was administered 2 hours after (but not concomitantly, 15 min, or 30 min after) the immediate-release aspirin dose [99.2%].

In another study, where immediate-release aspirin 81 mg was administered once daily with ibuprofen 400 mg given three times daily (1, 7, and 13 hours post-aspirin dose) for 10 consecutive days, the mean % serum thromboxane B2 (TxB2) inhibition suggested no interaction with the antiplatelet activity of aspirin [98.3%]. However, there were individual subjects with serum TxB2 inhibition below 95%, with the lowest being 90.2%.

When a similarly designed study was conducted with enteric-coated aspirin, where healthy subjects were administered enteric-coated aspirin 81 mg once daily for 6 days and ibuprofen 400 mg three times daily (2, 7 and 12 h post-aspirin dose) for 6 days, there was an interaction with the antiplatelet activity at 24 hours following the day-6 aspirin dose [67%] (see PRECAUTIONS-Drug Interactions).

Pharmacokinetics

Ibuprofen is a racemic mixture of [-]R-and [+]S-isomers.

In vivoand in vitrostudies indicate that the [+]S-isomer is responsible for clinical activity. The [-]R-form, while thought to be pharmacologically inactive, is slowly and incompletely (~ 60%) interconverted into the active [+]S species in adults. The degree of interconversion in children is unknown, but is thought to be similar. The [-]R-isomer serves as a circulating reservoir to maintain levels of active drug. Ibuprofen is well absorbed orally, with less than 1% being excreted in the urine unchanged. It has a biphasic elimination time curve with a plasma half-life of approximately 2 hours.

Studies in febrile children have established the dose-proportionality of 5 and 10 mg/kg doses of ibuprofen. Studies in adults have established the dose-proportionality of ibuprofen as a single oral dose from 50 to 600 mg for total drug and up to 1200 mg for free drug.

Absorption

In vivostudies indicate that ibuprofen is well absorbed orally from the suspension formulation, with peak plasma levels usually occurring within 1 to 2 hours (see Table 1).

Table 1 Pharmacokinetic Parameters of Ibuprofen Oral Suspension [Mean values (% coefficient of variation)]
Dose | 200 mg (2.8 mg/kg) in Adults | 10 mg/kg in Febrile Children
Formulation | Suspension | Suspension
Number of Patients | 24 | 18
AUCinf(mcg∙h/mL) | 64 (27%) | 155 (24%)
Cmax(mcg/mL) | 19 (22%) | 55 (23%)
Tmax(h) | 0.79 (69%) | 0.97 (57%)
Cl/F (mg/h/kg) | 45.6 (22%) | 68.6 (22%)
Legend:
AUCinf= Area-under-the-curve to infinity
Tmax= Time-to-peak plasma concentration
Cmax= Peak plasma concentration
Cl/F = Clearance divided by fraction at drug absorbed

Antacids

A bioavailability study in adults has shown that there was no interference with the absorption of ibuprofen when given in conjunction with an antacid containing both aluminum hydroxide and magnesium hydroxide.

H-2 Antagonists

In studies with human volunteers, coadministration of cimetidine or ranitidine with ibuprofen had no substantive effect on ibuprofen serum concentrations.

Food Effects

Absorption is most rapid when ibuprofen is given under fasting conditions.

Administration of ibuprofen with food affects the rate but not the extent of absorption. When taken with food, Tmaxis delayed by approximately 30 to 60 minutes, and peak levels are reduced by approximately 30 to 50%.

Distribution

Ibuprofen, like most drugs of its class, is highly protein bound (>99% bound at 20 mcg/mL). Protein binding is saturable and at concentrations >20 mcg/mL binding is non-linear. Based on oral dosing data there is an age- or fever-related change in volume of distribution for ibuprofen. Febrile children <11 years old have a volume of approximately 0.2 L/kg while adults have a volume of approximately 0.12 L/kg. The clinical significance of these findings is unknown.

Metabolism

Following oral administration, the majority of the dose was recovered in the urine within 24 hours as the hydroxy-(25%) and carboxypropyl-(37%) phenylpropionic acid metabolites. The percentages of free and conjugated ibuprofen found in the urine were approximately 1% and 14%, respectively. The remainder of the drug was found in the stool as both metabolites and unabsorbed drug.

Elimination

Ibuprofen is rapidly metabolized and eliminated in the urine. The excretion of ibuprofen is virtually complete 24 hours after the last dose. It has a biphasic plasma elimination time curve with a half-life of approximately 2 hours. There is no difference in the observed terminal elimination rate or half-life between children and adults, however, there is an age- or fever-related change in total clearance. This suggests that the observed change in clearance is due to changes in the volume of distribution of ibuprofen (see Table 1for Cl/F values).

Clinical Studies

Controlled clinical trials comparing doses of 5 and 10 mg/kg ibuprofen suspension and 10 to 15 mg/kg of acetaminophen elixir have been conducted in children 6 months to 12 years of age with fever primarily due to viral illnesses. In these studies there were no differences between treatments in fever reduction for the first hour and maximum fever reduction occurred between 2 and 4 hours. Response after 1 hour was dependent on both the level of temperature elevation as well as the treatment. In children with baseline temperatures at or below 102.5°F both ibuprofen doses and acetaminophen were equally effective in their maximum effect. In children with temperatures above 102.5°F, the ibuprofen 10 mg/kg dose was more effective. By 6 hours, children treated with ibuprofen 5 mg/kg tended to have recurrence of fever, whereas children treated with ibuprofen 10 mg/kg still had significant fever reduction at 8 hours. In control groups treated with 10 mg/kg acetaminophen, fever reduction resembled that seen in children treated with 5 mg/kg of ibuprofen, with the exception that temperature elevation tended to return 1 to 2 hours earlier.

In patients with primary dysmenorrhea, ibuprofen has been shown to reduce elevated levels of prostaglandin activity in the menstrual fluid and to reduce testing and active intrauterine pressure, as well as the frequency of uterine contractions. The probable mechanism of action is to inhibit prostaglandin synthesis rather than simply to provide analgesia.

INDICATIONS AND USAGE

Carefully consider the potential benefits and risks of ibuprofen oral suspension and other treatment options before deciding to use ibuprofen. Use the lowest effective dose for the shortest duration consistent with individual patient treatment goals (see WARNINGS).

In Pediatric Patients, Ibuprofen Oral Suspension is indicated:

- For reduction of fever in patients aged 6 months up to 2 years of age.
- For relief of mild to moderate pain in patients aged 6 months up to 2 years of age.
- For relief of signs and symptoms of juvenile arthritis.

In Adults, Ibuprofen Oral Suspension is indicated:

- For treatment of primary dysmenorrhea.
- For relief of the signs and symptoms of rheumatoid arthritis and osteoarthritis.

Since there have been no controlled trials to demonstrate whether there is any beneficial effect or harmful interaction with the use of ibuprofen in conjunction with aspirin, the combination cannot be recommended (see PRECAUTIONS-Drug Interactions).

CONTRAINDICATIONS

Ibuprofen oral suspension is contraindicated in patients with known hypersensitivity to ibuprofen.

Ibuprofen should not be given to patients who have experienced asthma, urticaria, or allergic-type reactions after taking aspirin or other NSAIDs. Severe, rarely fatal, anaphylactic-like reactions to NSAIDs have been reported in such patients (see WARNINGS-Anaphylactoid Reactions, and PRECAUTIONS-Preexisting Asthma).

Ibuprofen is contraindicated in the setting of coronary artery bypass graft (CABG) surgery (see WARNINGS).

WARNINGS

Cardiovascular Effects

Cardiovascular Thrombotic Events

Clinical trials of several COX-2 selective and nonselective NSAIDs of up to three years duration have shown an increased risk of serious cardiovascular (CV) thrombotic events, including myocardial infarction (MI) and stroke, which can be fatal. Based on available data, it is unclear that the risk for CV thrombotic events is similar for all NSAIDs. The relative increase in serious CV thrombotic events over baseline conferred by NSAID use appears to be similar in those with and without known CV disease or risk factors for CV disease. However, patients with known CV disease or risk factors had a higher absolute incidence of excess serious CV thrombotic events, due to their increased baseline rate. Some observational studies found that this increased risk of serious CV thrombotic events began as early as the first weeks of treatment. The increase in CV thrombotic risk has been observed most consistently at higher doses. To minimize the potential risk for an adverse CV event in NSAID-treated patients, use the lowest effective dose for the shortest duration possible. Physicians and patients should remain alert for the development of such events, throughout the entire treatment course, even in the absence of previous CV symptoms. Patients should be informed about the signs and/or symptoms of serious CV events and the steps to take if they occur.

There is no consistent evidence that concurrent use of aspirin mitigates the increased risk of serious CV thrombotic events associated with NSAID use. The concurrent use of aspirin and an NSAID, such as ibuprofen, increases the risk of serious gastrointestinal (GI) events (see WARNINGS).

Status Post Coronary Artery Bypass Graft (CABG) Surgery

Two large, controlled clinical trials of a COX-2 selective NSAID for the treatment of pain in the first 10 to 14 days following CABG surgery found an increased incidence of myocardial infarction and stroke. NSAIDs are contraindicated in the setting of CABG (see CONTRAINDICATIONS).

Post-MI Patients

Observational studies conducted in the Danish National Registry have demonstrated that patients treated with NSAIDs in the post-MI period were at increased risk of reinfarction, CV-related death, and all-cause mortality beginning in the first week of treatment. In this same cohort, the incidence of death in the first year post MI was 20 per 100 person years in NSAID-treated patients compared to 12 per 100 person years in non-NSAID exposed patients. Although the absolute rate of death declined somewhat after the first year post-MI, the increased relative risk of death in NSAID users persisted over at least the next four years of follow-up.

Avoid the use of ibuprofen oral suspension in patients with a recent MI unless the benefits are expected to outweigh the risk of recurrent CV thrombotic events. If ibuprofen oral suspension is used in patients with a recent MI, monitor patients for signs of cardiac ischemia.

Hypertension

NSAIDs, including ibuprofen, can lead to onset of new hypertension or worsening of pre-existing hypertension, either of which may contribute to the increased incidence of CV events. Patients taking thiazides or loop diuretics may have impaired response to these therapies when taking NSAIDs. NSAIDs, including ibuprofen, should be used with caution in patients with hypertension. Blood pressure (BP) should be monitored closely during the initiation of NSAID treatment and throughout the course of therapy.

Heart Failure and Edema

The Coxib and traditional NSAID Trialists' Collaboration meta-analysis of randomized controlled trials demonstrated an approximately 2-fold increase in hospitalizations for heart failure in COX-2 selective-treated patients and nonselective NSAID-treated patients compared to placebo-treated patients. In a Danish National Registry study of patients with heart failure, NSAID use increased the risk of MI, hospitalization for heart failure, and death.

Additionally, fluid retention and edema have been observed in some patients treated with NSAIDs. Use of ibuprofen may blunt the CV effects of several therapeutic agents used to treat these medical conditions [e.g., diuretics, ACE inhibitors, or angiotensin receptor blockers (ARBs)] (see Drug Interactions).

Avoid the use of ibuprofen oral suspension in patients with severe heart failure unless the benefits are expected to outweigh the risk of worsening heart failure. If ibuprofen oral suspension is used in patients with severe heart failure, monitor patients for signs of worsening heart failure.

Gastrointestinal Effects

Risk of Ulceration, Bleeding, and Perforation

NSAIDs, including ibuprofen, can cause serious gastrointestinal (GI) adverse events including inflammation, bleeding, ulceration, and perforation of the stomach, small intestine, or large intestine, which can be fatal. These serious adverse events can occur at any time, with or without warning symptoms, in patients treated with NSAIDs. Only one in five patients, who develop a serious upper GI adverse event on NSAID therapy, is symptomatic. Upper GI ulcers, gross bleeding, or perforation caused by NSAIDs occur in approximately 1% of patients treated for 3 to 6 months, and in about 2 to 4% of patients treated for one year. These trends continue with longer duration of use, increasing the likelihood of developing a serious GI event at some time during the course of therapy. However, even short-term therapy is not without risk. NSAIDs should be prescribed with extreme caution in those with a prior history of ulcer disease or gastrointestinal bleeding. Patients with a prior history of peptic ulcer disease and/or gastrointestinal bleedingwho use NSAIDs have a greater than 10-fold risk for developing a GI bleed compared to patients with neither of these risk factors. Other factors that increase the risk for GI bleeding in patients treated with NSAIDs include concomitant use of oral corticosteroids or anticoagulants, longer duration of NSAID therapy, smoking, use of alcohol, older age, and poor general health status. Most spontaneous reports of fatal GI events are in elderly or debilitated patients and therefore, special care should be taken in treating this population. To minimize the potential risk for an adverse GI event in patients treated with an NSAID, the lowest effective dose should be used for the shortest possible duration. Patients and physicians should remain alert for signs and symptoms of GI ulceration and bleeding during NSAID therapy and promptly initiate additional evaluation and treatment if a serious GI adverse event is suspected. This should include discontinuation of the NSAID until a serious GI adverse event is ruled out. For high risk patients, alternate therapies that do not involve NSAIDs should be considered.

Renal Effects

Long-term administration of NSAIDs has resulted in renal papillary necrosis and other renal injury. Renal toxicity has also been seen in patients in whom renal prostaglandins have a compensatory role in the maintenance of renal perfusion. In these patients, administration of a nonsteroidal anti-inflammatory drug may cause a dose-dependent reduction in prostaglandin formation and, secondarily, in renal blood flow, which may precipitate overt renal decompensation. Patients at greatest risk of this reaction are those with impaired renal function, heart failure, liver dysfunction, those taking diuretics and ACE inhibitors, and the elderly. Discontinuation of NSAID therapy is usually followed by recovery to the pretreatment state.

Advanced Renal Disease

No information is available from controlled clinical studies regarding the use of ibuprofen in patients with advanced renal disease. Therefore, treatment with ibuprofen is not recommended in these patients with advanced renal disease. If ibuprofen therapy must be initiated, close monitoring of the patient's renal function is advisable.

Anaphylactoid Reactions

As with other NSAIDs, anaphylactoid reactions may occur in patients without known prior exposure to ibuprofen. Ibuprofen should not be given to patients with the aspirin triad. This symptom complex typically occurs in asthmatic patients who experience rhinitis with or without nasal polyps, or who exhibit severe, potentially fatal bronchospasm after taking aspirin or other NSAIDs (see CONTRAINDICATIONSand PRECAUTIONS-Preexisting Asthma). Emergency help should be sought in cases where an anaphylactoid reaction occurs.

Serious Skin Reactions

NSAIDs, including ibuprofen, can cause serious skin adverse reactions such as exfoliative dermatitis, Stevens-Johnson Syndrome (SJS), and toxic epidermal necrolysis (TEN), which can be fatal. NSAIDs can also cause fixed drug eruption (FDE). FDE may present as a more severe variant known as generalized bullous fixed drug eruption (GBFDE), which can be life-threatening. These serious events may occur without warning. Inform patients about the signs and symptoms of serious skin reactions, and to discontinue the use of ibuprofen oral suspension at the first appearance of skin rash or any other sign of hypersensitivity. Ibuprofen oral suspension is contraindicated in patients with previous serious skin reactions to NSAIDs (see CONTRAINDICATIONS).

Drug Reaction with Eosinophilia and Systemic Symptoms (DRESS) has been reported in patients taking NSAIDs such as ibuprofen oral suspension. Some of these events have been fatal or life-threatening. DRESS typically, although not exclusively, presents with fever, rash, lymphadenopathy, and/or facial swelling. Other clinical manifestations may include hepatitis, nephritis, hematological abnormalities, myocarditis, or myositis. Sometimes symptoms of DRESS may resemble an acute viral infection. Eosinophilia is often present. Because this disorder is variable in its presentation, other organ systems not noted here may be involved. It is important to note that early manifestations of hypersensitivity, such as fever or lymphadenopathy, may be present even though rash is not evident. If such signs or symptoms are present, discontinue ibuprofen oral suspension and evaluate the patient immediately.

Fetal Toxicity

Premature Closure of Fetal Ductus Arteriosus

Avoid use of NSAIDs, including ibuprofen oral suspension, in pregnant women at about 30 weeks gestation and later. NSAIDs including ibuprofen oral suspension, increase the risk of premature closure of the fetal ductus arteriosus at approximately this gestational age.

Oligohydramnios/Neonatal Renal Impairment

Use of NSAIDs, including ibuprofen oral suspension, at about 20 weeks gestation or later in pregnancy may cause fetal renal dysfunction leading to oligohydramnios and, in some cases, neonatal renal impairment. These adverse outcomes are seen, on average, after days to weeks of treatment, although oligohydramnios has been infrequently reported as soon as 48 hours after NSAID initiation. Oligohydramnios is often, but not always, reversible with treatment discontinuation. Complications of prolonged oligohydramnios may, for example, include limb contractures and delayed lung maturation. In some postmarketing cases of impaired neonatal renal function, invasive procedures such as exchange transfusion or dialysis were required.

If NSAID treatment is necessary between about 20 weeks and 30 weeks gestation, limit ibuprofen use to the lowest effective dose and shortest duration possible. Consider ultrasound monitoring of amniotic fluid if ibuprofen treatment extends beyond 48 hours. Discontinue ibuprofen if oligohydramnios occurs and follow up according to clinical practice [ see PRECAUTIONS; Pregnancy] .

PRECAUTIONS

General

Ibuprofen cannot be expected to substitute for corticosteroids or to treat corticosteroid insufficiency. Abrupt discontinuation of corticosteroids may lead to disease exacerbation. Patients on prolonged corticosteroid therapy should have their therapy tapered slowly if a decision is made to discontinue corticosteroids. The pharmacological activity of ibuprofen in reducing fever and inflammation may diminish the utility of these diagnostic signs in detecting complications of presumed noninfectious, painful conditions.

Hepatic Effects

Borderline elevations of one or more liver tests may occur in up to 15% of patients taking NSAIDs including ibuprofen. These laboratory abnormalities may progress, may remain unchanged, or may be transient with continuing therapy. Notable elevations of ALT or AST (approximately three or more times the upper limit of normal) have been reported in approximately 1% of patients in clinical trials with NSAIDs. In addition, rare cases of severe hepatic reactions, including jaundice and fatal fulminant hepatitis, liver necrosis and hepatic failure, some of them with fatal outcomes have been reported.

A patient with symptoms and/or signs suggesting liver dysfunction, or in whom an abnormal liver test has occurred, should be evaluated for evidence of the development of a more severe hepatic reaction while on therapy with ibuprofen. If clinical signs and symptoms consistent with liver disease develop, or if systemic manifestations occur (e.g., eosinophilia, rash, etc.), ibuprofen should be discontinued.

Hematological Effects

Anemia is sometimes seen in patients receiving NSAIDs, including ibuprofen. This may be due to fluid retention, occult or gross GI blood loss, or an incompletely described effect upon erythropoiesis. Patients on long-term treatment with NSAIDs, including ibuprofen, should have their hemoglobin or hematocrit checked if they exhibit any signs or symptoms of anemia.

In two postmarketing clinical studies the incidence of a decreased hemoglobin level was greater than previously reported. Decrease in hemoglobin of 1 gram or more was observed in 17.1% of 193 patients on 1600 mg ibuprofen daily (osteoarthritis), and in 22.8% of 189 patients taking 2400 mg of ibuprofen daily (rheumatoid arthritis). Positive stool occult blood tests and elevated serum creatinine levels were also observed in these studies.

NSAIDs inhibit platelet aggregation and have been shown to prolong bleeding time in some patients. Unlike aspirin, their effect on platelet function is quantitatively less, of shorter duration, and reversible. Patients receiving ibuprofen who may be adversely affected by alterations in platelet function, such as those with coagulation disorders or patients receiving anticoagulants, should be carefully monitored.

Preexisting Asthma

Patients with asthma may have aspirin-sensitive asthma. The use of aspirin in patients with aspirin-sensitive asthma has been associated with severe bronchospasm, which can be fatal. Since cross reactivity, including bronchospasm, between aspirin and other nonsteroidal anti-inflammatory drugs has been reported in such aspirin-sensitive patients, ibuprofen should not be administered to patients with this form of aspirin sensitivity and should be used with caution in patients with preexisting asthma.

Aseptic Meningitis

Aseptic meningitis, with fever and coma, has been observed on rare occasions in patients on ibuprofen therapy. Although it is probably more likely to occur in patients with systemic lupus erythematosus and related connective tissue diseases, it has been reported in patients who do not have an underlying chronic disease.

Diabetics

Ibuprofen oral suspension contains 0.3 g sucrose and 1.6 calories per mL, or 1.5 g sucrose and 8 calories per teaspoon, which should be taken into consideration when treating diabetic patients with this product.

Information for Patients

Patients should be informed of the following information before initiating therapy with an NSAID and periodically during the course of ongoing therapy. Patients should also be encouraged to read the NSAID Medication Guide that accompanies each prescription dispensed.

1. Cardiovascular Thrombotic Events
  Advise patients to be alert for the symptoms of cardiovascular thrombotic events, including chest pain, shortness of breath, weakness, or slurring of speech, and to report any of these symptoms to their healthcare provider immediately (see WARNINGS).
2. Ibuprofen, like other NSAIDs, can cause GI discomfort and, rarely, serious GI side effects, such as ulcers and bleeding, which may result in hospitalization or even death. Although serious GI tract ulcerations and bleeding can occur without warning symptoms, patients should be alert for signs and symptoms of ulcerations and bleeding, and should ask for medical advice when observing any indicative sign or symptoms including epigastric pain, dyspepsia, melena, and hematemesis. Patients should be apprised of the importance of this follow-up (see WARNINGS, Gastrointestinal Effects-Risk of Ulceration, Bleeding, and Perforation).
3. Serious Skin Reactions, including DRESS
  Advise patients to stop taking ibuprofen oral suspension immediately if they develop any type of rash or fever and to contact their healthcare provider as soon as possible [see WARNINGS].
4. Heart Failure and Edema
  Advise patients to be alert for the symptoms of congestive heart failure including shortness of breath, unexplained weight gain, or edema and to contact their healthcare provider if such symptoms occur (see WARNINGS).
5. Patients should be informed of the warning signs and symptoms of hepatotoxicity (e.g., nausea, fatigue, lethargy, pruritus, jaundice, right upper quadrant tenderness, and "flu-like" symptoms). If these occur, patients should be instructed to stop therapy and seek immediate medical therapy.
6. Patients should be informed of the signs of an anaphylactoid reaction (e.g., difficulty breathing, swelling of the face or throat). If these occur, patients should be instructed to seek immediate emergency help (see WARNINGS).
7. Fetal Toxicity
  Inform pregnant women to avoid use of ibuprofen oral suspension and other NSAIDs starting at 30 weeks gestation because of the risk of the premature closing of the fetal ductus arteriosus. If treatment with ibuprofen oral suspension is needed for a pregnant woman between about 20 to 30 weeks gestation, advise her that she may need to be monitored for oligohydramnios, if treatment continues for longer than 48 hours [ see WARNINGS; Fetal Toxicity, PRECAUTIONS; Pregnancy] .

Laboratory Tests

Because serious GI tract ulcerations and bleeding can occur without warning symptoms, physicians should monitor for signs or symptoms of GI bleeding. Patients on long-term treatment with NSAIDs should have their CBC and a chemistry profile checked periodically. If clinical signs and symptoms consistent with liver or renal disease develop, systemic manifestations occur (e.g., eosinophilia, rash, etc.) or if abnormal liver tests persist or worsen, ibuprofen should be discontinued.

Drug Interactions

ACE-Inhibitors

Reports suggest that NSAIDs may diminish the antihypertensive effect of ACE-inhibitors. This interaction should be given consideration in patients taking NSAIDs concomitantly with ACE-inhibitors.

Aspirin

Pharmacodynamic studies have demonstrated interference with the antiplatelet activity of aspirin when ibuprofen 400 mg, given three times daily, is administered with enteric-coated low-dose aspirin. The interaction exists even following a once-daily regimen of ibuprofen 400 mg, particularly when ibuprofen is dosed prior to aspirin. The interaction is alleviated if immediate-release low-dose aspirin is dosed at least 2 hours prior to a once-daily regimen of ibuprofen; however, this finding cannot be extended to enteric-coated low-dose aspirin (see CLINICAL PHARMACOLOGY-Pharmacodynamics) .

Because there may be an increased risk of cardiovascular events due to the interference of ibuprofen with the antiplatelet effect of aspirin, for patients taking low-dose aspirin for cardioprotection who require analgesics, consider use of an NSAID that does not interfere with the antiplatelet effect of aspirin, or non-NSAID analgesics, where appropriate.

As with other NSAIDs, concomitant administration of ibuprofen and aspirin is not generally recommended because of the potential of increased adverse effects.

Diuretics

Clinical studies, as well as post marketing observations, have shown that ibuprofen can reduce the natriuretic effect of furosemide and thiazides in some patients. This response has been attributed to inhibition of renal prostaglandin synthesis. During concomitant therapy with NSAIDs, the patient should be observed closely for signs of renal failure (see WARNINGS, Renal Effects), as well as to assure diuretic efficacy.

Lithium

Ibuprofen produced an elevation of plasma lithium levels and a reduction in renal lithium clearance in a study of eleven normal volunteers. The mean minimum lithium concentration increased 15% and the renal clearance of lithium was decreased by 19% during this period of concomitant drug administration. This effect has been attributed to inhibition of renal prostaglandin synthesis by ibuprofen. Thus, when ibuprofen and lithium are administered concurrently, subjects should be observed carefully for signs of lithium toxicity. (Read circulars for lithium preparation before use of such concurrent therapy.)

Methotrexate

NSAIDs have been reported to competitively inhibit methotrexate accumulation in rabbit kidney slices. This may indicate that they could enhance the toxicity of methotrexate. Caution should be used when NSAIDs are administered concomitantly with methotrexate.

Warfarin

Several short-term controlled studies failed to show that ibuprofen significantly affected prothrombin times or a variety of other clotting factors when administered to individuals on warfarin-type anticoagulants. However, because bleeding has been reported when ibuprofen and other NSAIDs have been administered to patients on warfarin-type anticoagulants, the physician should be cautious when administering ibuprofen to patients on anticoagulants. The effects of warfarin and NSAIDs on GI bleeding are synergistic, such that the users of both drugs together have a risk of serious GI bleeding higher than users of either drug alone.

Pregnancy

Risk Summary

Use of NSAIDs, including ibuprofen oral suspension, can cause premature closure of the fetal ductus arteriosus and fetal renal dysfunction leading to oligohydramnios and, in some cases, neonatal renal impairment. Because of these risks, limit dose and duration of ibuprofen oral suspension use between about 20 and 30 weeks of gestation, and avoid ibuprofen use at about 30 weeks of gestation and later in pregnancy (see WARNINGS; Fetal Toxicity).

Premature Closure of Fetal Ductus Arteriosus

Use of NSAIDs, including ibuprofen oral suspension, at about 30 weeks gestation or later in pregnancy increases the risk of premature closure of the fetal ductus arteriosus.

Oligohydramnios/Neonatal Renal Impairment

Use of NSAIDs at about 20 weeks gestation or later in pregnancy has been associated with cases of fetal renal dysfunction leading to oligohydramnios, and in some cases, neonatal renal impairment.

Data from observational studies regarding other potential embryo-fetal risks of NSAID use in women in the first or second trimesters of pregnancy are inconclusive.

Reproductive studies conducted in rats and rabbits have not demonstrated evidence of developmental abnormalities. However, animal reproduction studies are not always predictive of human response. Based on animal data, prostaglandins have been shown to have an important role in endometrial vascular permeability, blastocyst implantation, and decidualization. In animal studies, administration of prostaglandin synthesis inhibitors such as ibuprofen, resulted in increased pre- and post-implantation loss. Prostaglandins also have been shown to have an important role in fetal kidney development. In published animal studies, prostaglandin synthesis inhibitors have been reported to impair kidney development when administered at clinically relevant doses.

The estimated background risk of major birth defects and miscarriage for the indicated population(s) is unknown. All pregnancies have a background risk of birth defect, loss, or other adverse outcomes. In the U.S. general population, the estimated background risk of major birth defects and miscarriage in clinically recognized pregnancies is 2 to 4% and 15 to 20%, respectively.

Clinical Considerations

Fetal/Neonatal Adverse Reactions

Premature Closure of Fetal Ductus Arteriosus

Avoid use of NSAIDs in women at about 30 weeks gestation and later in pregnancy, because NSAIDs, including ibuprofen oral suspension, can cause premature closure of the fetal ductus arteriosus (see WARNINGS; Fetal Toxicity) .

Oligohydramnios/Neonatal Renal Impairment

If an NSAID is necessary at about 20 weeks gestation or later in pregnancy, limit the use to the lowest effective dose and shortest duration possible. If ibuprofen oral suspension treatment extends beyond 48 hours, consider monitoring with ultrasound for oligohydramnios. If oligohydramnios occurs, discontinue ibuprofen oral suspension and follow up according to clinical practice (see WARNINGS; Fetal Toxicity) .

Data

Human Data

There are no adequate and well-controlled studies in pregnant women. Ibuprofen should be used in pregnancy only if the potential benefit justifies the potential risk to the fetus.

Premature Closure of Fetal Ductus Arteriosus

Published literature reports that the use of NSAIDs at about 30 weeks of gestation and later in pregnancy may cause premature closure of the fetal ductus arteriosus.

Oligohydramnios/Neonatal Renal Impairment

Published studies and postmarketing reports describe maternal NSAID use at about 20 weeks gestation or later in pregnancy associated with fetal renal dysfunction leading to oligohydramnios, and in some cases, neonatal renal impairment. These adverse outcomes are seen, on average, after days to weeks of treatment, although oligohydramnios has been infrequently reported as soon as 48 hours after NSAID initiation. In many cases, but not all, the decrease in amniotic fluid was transient and reversible with cessation of the drug. There have been a limited number of case reports of maternal NSAID use and neonatal renal dysfunction without oligohydramnios, some of which were irreversible. Some cases of neonatal renal dysfunction required treatment with invasive procedures, such as exchange transfusion or dialysis.

Methodological limitations of these postmarketing studies and reports include lack of a control group; limited information regarding dose, duration, and timing of drug exposure; and concomitant use of other medications. These limitations preclude establishing a reliable estimate of the risk of adverse fetal and neonatal outcomes with maternal NSAID use. Because the published safety data on neonatal outcomes involved mostly preterm infants, the generalizability of certain reported risks to the full-term infant exposed to NSAIDs through maternal use is uncertain.

Labor and Delivery

In rat studies with NSAIDs, as with other drugs known to inhibit prostaglandin synthesis, an increased incidence of dystocia, delayed parturition, and decreased pup survival occurred. The effects of ibuprofen on labor and delivery in pregnant women are unknown. Therefore, administration of ibuprofen is not recommended during labor and delivery.

Nursing Mothers

It is not known whether this drug is excreted in human milk. Because many drugs are excreted in human milk and because of the potential for serious adverse reactions in nursing infants from ibuprofen, a decision should be made whether to discontinue nursing or to discontinue the drug, taking into account the importance of the drug to the mother.

Pediatric Use

Safety and effectiveness of ibuprofen in pediatric patients below the age of 6 months have not been established (see CLINICAL PHARMACOLOGY-Clinical Studies). Dosing of ibuprofen in children 6 months or older should be guided by their body weight (see DOSAGE AND ADMINISTRATION).

Geriatric Use

As with any NSAIDs, caution should be exercised in treating the elderly (65 years and older).

ADVERSE REACTIONS

In patients taking ibuprofen or other NSAIDs, the most frequently reported adverse experiences occurring in approximately 1 to 10% of patients are: Abnormal renal function, anemia, dizziness, edema, elevated liver enzymes, fluid retention, gastrointestinal experiences (including abdominal pain, bloating, constipation, diarrhea, dyspepsia, epigastric pain, flatulence, heartburn, nausea, vomiting), headaches, increased bleeding time, nervousness, pruritus, rashes (including maculopapular) and tinnitus.

Additional adverse experiences reported occasionally include:

Body as a whole- fever, infection, sepsis

Cardiovascular system- congestive heart failure in patients with marginal cardiac function, hypertension, tachycardia, syncope

Digestive system- dry mouth, duodenitis, esophagitis, gastric or duodenal ulcer with bleeding and/or perforation, gastritis, gastrointestinal bleeding, glossitis, hematemesis, hepatitis, jaundice, melena, rectal bleeding

Hemic and lymphatic system- ecchymosis, eosinophilia, leukopenia, purpura, stomatitis, thrombocytopenia

Metabolic and nutritional- weight changes

Nervous system- anxiety, asthenia, confusion, depression, dream abnormalities, drowsiness, insomnia, malaise, paresthesia, somnolence, tremors, vertigo

Respiratory system- asthma, dyspnea

Skin and appendages- alopecia, photosensitivity, sweat

Special senses- blurred vision

Urogenital system- cystitis, dysuria, hematuria, interstitial nephritis, oliguria/polyuria, proteinuria, acute renal failure in patients with pre-existing significantly impaired renal function

Other adverse reactions, which occur rarely are:

Body as a whole- anaphylactic reactions, anaphylactoid reactions, appetite changes

Cardiovascular system- arrhythmia, cerebrovascular accident, hypotension, myocardial infarction, palpitations, vasculitis

Digestive system- eructation, gingival ulcer, hepatorenal syndrome, liver necrosis, liver failure, pancreatitis

Hemic and lymphatic system- agranulocystosis, hemolytic anemia, aplastic anemia, lymphadenopathy, neutropenia, pancytopenia

Metabolic and nutritional- hyperglycemia

Nervous system- convulsions, coma, emotional liability hallucinations, aseptic meningitis

Respiratory- apnea, respiratory depression, pneumonia, rhinitis

Skin and appendages- angioedema, toxic epidermal necrosis, erythema multiforme, exfoliative dermatitis, Stevens Johnson Syndrome, fixed drug eruption (FDE), urticaria, vesiculobullous eruptions

Special senses- amblyopia (blurred and/or diminished vision, scotomata and/or changes in color vision), conjunctivitis, dry eyes, hearing impairment

Urogenital- azotemia, decreased creatinine clearance, glomerulitis, renal papillary necrosis, tubular necrosis

To report SUSPECTED ADVERSE EVENTS, contact Sun Pharmaceutical Industries, Inc., at 1-866-923-4914 or FDA at 1-800-FDA-1088 or http://www.fda.gov/medwatch for voluntary reporting of adverse reactions.

OVERDOSAGE

The toxicity of ibuprofen overdose is dependent upon the amount of drug ingested and the time elapsed since ingestion, though individual response may vary, which makes it necessary to evaluate each case individually. Although uncommon, serious toxicity and death have been reported in the medical literature with ibuprofen overdosage. The most frequently reported symptoms of ibuprofen overdose include abdominal pain, nausea, vomiting, lethargy and drowsiness. Other central nervous system symptoms include headache, tinnitus, CNS depression and seizures. Metabolic acidosis, coma, acute renal failure and apnea (primarily in very young children) may rarely occur. Cardiovascular toxicity, including hypotension, bradycardia, tachycardia and atrial fibrillation also have been reported.

The treatment of acute ibuprofen overdose is primarily supportive. Management of hypotension, acidosis and gastrointestinal bleeding may be necessary.

In cases of acute overdose, the stomach should be emptied through ipecac-induced emesis or lavage. Emesis is most effective if initiated within 30 minutes of ingestion. Orally administered activated charcoal may help in reducing the absorption and reabsorption of ibuprofen.

In children, the estimated amount of ibuprofen ingested per body weight may be helpful to predict the potential for development of toxicity although each case must be evaluated. Ingestion of less than 100 mg/kg is unlikely to produce toxicity. Children ingesting 100 to 200 mg/kg may be managed with induced emesis and a minimal observation time of four hours. Children ingesting 200 to 400 mg/kg of ibuprofen should have immediate gastric emptying and at least four hours observation in a health care facility. Children ingesting greater than 400 mg/kg require immediate medical referral, careful observation and appropriate supportive therapy. Ipecac-induced emesis is not recommended in overdoses greater than 400 mg/kg because of the risk for convulsions and the potential for aspiration of gastric contents.

In adult patients the history of the dose reportedly ingested does not appear to be predictive of toxicity. The need for referral and follow-up must be judged by the circumstances at the time of the overdose ingestion. Symptomatic adults should be carefully evaluated, observed and supported.

DOSAGE AND ADMINISTRATION

Carefully consider the potential benefits and risks of ibuprofen oral suspension and other treatment options before deciding to use ibuprofen oral suspension. Use the lowest effective dose for the shortest duration consistent with individual patient treatment goals (see WARNINGS).

After observing the response to initial therapy with ibuprofen oral suspension, the dose and frequency should be adjusted to suit an individual patient's needs.

Pediatric Patients

Fever Reduction

For reduction of fever in children, 6 months up to 2 years of age, the dosage should be adjusted on the basis of the initial temperature level (see CLINICAL PHARMACOLOGY). The recommended dose is 5 mg/kg if the baseline temperature is less than 102.5ºF, or 10 mg/kg if the baseline temperature is 102.5ºF or greater. The duration of fever reduction is generally 6 to 8 hours. The recommended maximum daily dose is 40 mg/kg.

Analgesia

For relief of mild to moderate pain in children 6 months up to 2 years of age, the recommended dosage is 10 mg/kg, every 6 to 8 hours. The recommended maximum daily dose is 40 mg/kg. Doses should be given so as not to disturb the child's sleep pattern.

Juvenile Arthritis

The recommended dose is 30 to 40 mg/kg/day divided into three to four doses (see Individualization of Dosage). Patients with milder disease may be adequately treated with 20 mg/kg/day. In patients with juvenile arthritis, doses above 50 mg/kg/day are not recommended because they have not been studied and doses exceeding the upper recommended dose of 40 mg/kg/day may increase the risk of causing serious adverse events. The therapeutic response may require from a few days to several weeks to be achieved. Once a clinical effect is obtained, the dosage should be lowered to the smallest dose of ibuprofen oral suspension needed to maintain adequate control of symptoms.

Pediatric patients receiving doses above 30 mg/kg/day or if abnormal liver function tests have occurred with previous NSAID treatments should be carefully followed for signs and symptoms of early liver dysfunction.

Adults

Primary Dysmenorrhea

For the treatment of primary dysmenorrhea, beginning with the earliest onset of such pain, ibuprofen oral suspension should be given in a dose of 400 mg every 4 hours, as necessary, for the relief of pain.

Rheumatoid Arthritis and Osteoarthritis

Suggested dosage: 1200 to 3200 mg daily (300 mg q.i.d. or 400 mg, 600 mg or 800 mg t.i.d. or q.i.d.). Individual patients may show a better response to 3200 mg daily, as compared with 2400 mg, although in well-controlled clinical trials patients on 3200 mg did not show a better mean response in terms of efficacy. Therefore, when treating patients with 3200 mg/day, the physician should observe sufficient increased clinical benefits to offset potential increased risk.

Individualization of Dosage

The dose of ibuprofen oral suspension should be tailored to each patient, and may be lowered or raised from the suggested doses depending on the severity of symptoms either at time of initiating drug therapy or as the patient responds or fails to respond. One fever study showed that, after the initial dose of ibuprofen oral suspension, subsequent doses may be lowered and still provide adequate fever control.

In a situation when low fever would require the ibuprofen oral suspension 5 mg/kg dose in a child with pain, the dose that will effectively treat the predominant symptom should be chosen. In chronic conditions, a therapeutic response to ibuprofen therapy is sometimes seen in a few days to a week, but most often is observed by two weeks. After a satisfactory response has been achieved, the patient's dose should be reviewed and adjusted as required. Patients with rheumatoid arthritis seem to require higher doses than do patients with osteoarthritis. The smallest dose of ibuprofen oral suspension that yields acceptable control should be employed. Ibuprofen oral suspension may be used in combination with gold salts and/or corticosteroids.

HOW SUPPLIED

Ibuprofen Oral Suspension USP, 100 mg/5 mL

White to off-white, berry-flavored suspension

- Bottles of 4 fl oz (118 mL) - NDC 51672-1385-8

- Bottles of ONE PINT (473 mL) - NDC 51672-1385-9

STORAGE AND HANDLING

Shake well before using. Store at 20° to 25°C (68° to 77°F) [see USP Controlled Room Temperature].

Dispense in a well-closed container as defined in the USP.

Manufactured by: Sun Pharma Canada Inc., Brampton, Ontario, Canada L6T 1C1
Distributed by: Sun Pharmaceutical Industries, Inc., Cranbury, NJ 28512
Revised: December 2025
5264922-1225-01 32

Medication Guide for Nonsteroidal Anti-inflammatory Drugs (NSAIDs)

What is the most important information I should know about medicines called Nonsteroidal Anti-inflammatory Drugs (NSAIDs)?

NSAIDs can cause serious side effects, including:

- Increased risk of a heart attack or stroke that can lead to death.This risk may happen early in treatment and may increase:
  - with increasing doses of NSAIDs
  - with longer use of NSAIDs

Do not take NSAIDs right before or after a heart surgery called a "coronary artery bypass graft (CABG)."

Avoid taking NSAIDs after a recent heart attack, unless your healthcare provider tells you to. You may have an increased risk of another heart attack if you take NSAIDs after a recent heart attack.

- Increased risk of bleeding, ulcers, and tears (perforation) of the esophagus (tube leading from the mouth to the stomach), stomach and intestines:
  - anytime during use
  - without warning symptoms
  - that may cause death

The risk of getting an ulcer or bleeding increases with:

- past history of stomach ulcers, or stomach or intestinal bleeding with use of NSAIDs
- taking medicines called "corticosteroids", "anticoagulants", "SSRIs", or "SNRIs"

- increasing doses of NSAIDs
- longer use of NSAIDs
- smoking
- drinking alcohol

- older age
- poor health
- advanced liver disease
- bleeding problems

NSAIDs should only be used:

- exactly as prescribed
- at the lowest dose possible for your treatment
- for the shortest time needed

What are NSAIDs?

NSAIDs are used to treat pain and redness, swelling, and heat (inflammation) from medical conditions such as different types of arthritis, menstrual cramps, and other types of short-term pain.

Who should not take NSAIDs?

Do not take NSAIDs:

- if you have had an asthma attack, hives, or other allergic reaction with aspirin or any other NSAIDs.
- right before or after heart bypass surgery.

Before taking NSAIDs, tell your healthcare provider about all of your medical conditions, including if you:

- have liver or kidney problems
- have high blood pressure
- have asthma
- are pregnant or plan to become pregnant. Taking NSAIDs at about 20 weeks of pregnancy or later may harm your unborn baby. If you need to take NSAIDs for more than 2 days when you are between 20 and 30 weeks of pregnancy, your healthcare provider may need to monitor the amount of fluid in your womb around your baby. Talk to your healthcare provider if you are considering taking NSAIDs during pregnancy. You should not take NSAIDs after about 30 weeks of pregnancy.
- are breastfeeding or plan to breastfeed.

Tell your healthcare provider about all of the medicines you take, including prescription or over-the-counter medicines, vitamins or herbal supplements.NSAIDs and some other medicines can interact with each other and cause serious side effects. Do not start taking any new medicine without talking to your healthcare provider first.

What are the possible side effects of NSAIDs?

NSAIDs can cause serious side effects, including:

See " What is the most important information I should know about medicines called Nonsteroidal Anti-inflammatory Drugs (NSAIDs)?"

- new or worse high blood pressure
- heart failure
- liver problems including liver failure
- kidney problems including kidney failure
- low red blood cells (anemia)
- life-threatening skin reactions
- life-threatening allergic reactions
- Other side effects of NSAIDs include:stomach pain, constipation, diarrhea, gas, heartburn, nausea, vomiting, and dizziness.

Get emergency help right away if you get any of the following symptoms:

- shortness of breath or trouble breathing
- chest pain
- weakness in one part or side of your body
- slurred speech
- swelling of the face or throat

Stop taking your NSAID and call your healthcare provider right away if you get any of the following symptoms:

- nausea
- more tired or weaker than usual
- diarrhea
- itching
- your skin or eyes look yellow
- indigestion or stomach pain
- vomit blood
- there is blood in your bowel movement or it is black and sticky like tar
- unusual weight gain
- skin rash or blisters with fever
- swelling of the arms, legs, hands and feet
- flu-like symptoms

If you take too much of your NSAID, call your healthcare provider or get medical help right away.

These are not all the possible side effects of NSAIDs. For more information, ask your healthcare provider or pharmacist about NSAIDs.

Call your doctor for medical advice about side effects. You may report side effects to FDA at 1-800-FDA-1088.

Other information about NSAIDs

- Aspirin is an NSAID but it does not increase the chance of a heart attack. Aspirin can cause bleeding in the brain, stomach, and intestines. Aspirin can also cause ulcers in the stomach and intestines.
- Some NSAIDs are sold in lower doses without a prescription (over-the-counter). Talk to your healthcare provider before using over-the-counter NSAIDs for more than 10 days.

General information about the safe and effective use of NSAIDs

Medicines are sometimes prescribed for purposes other than those listed in a Medication Guide. Do not use NSAIDs for a condition for which it was not prescribed. Do not give NSAIDs to other people, even if they have the same symptoms that you have. It may harm them.

If you would like more information about NSAIDs, talk with your healthcare provider. You can ask your pharmacist or healthcare provider for information about NSAIDs that is written for health professionals.

For more information, call Sun Pharmaceutical Industries, Inc. at 1-866-923-4914.

This Medication Guide has been approved by the U.S. Food and Drug Administration.

Manufactured by: Sun Pharma Canada Inc., Brampton, Ontario, Canada L6T 1C1
Distributed by: Sun Pharmaceutical Industries, Inc., Cranbury, NJ 28512
Revised: December 2025
5264922-1225-01 32

PRINCIPAL DISPLAY PANEL - 118 mL Bottle Carton

NDC 51672-1385-8

Ibuprofen
Oral Suspension USP

100 mg / 5 mL

ATTENTION
PHARMACIST:
Dispense the
accompanying
Medication Guide to
each patient.

Dosage Cup
Included

4 fl oz
(118 mL)

Rx only
TARO